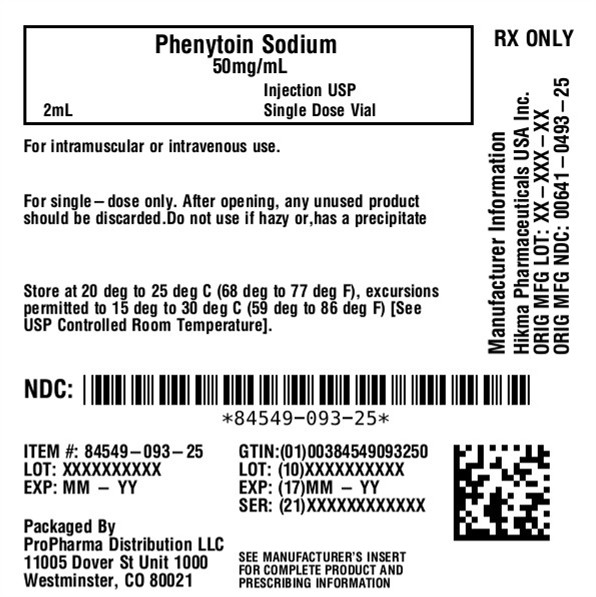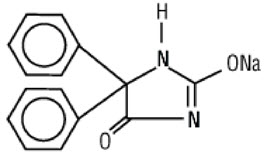 DRUG LABEL: Phenytoin Sodium
NDC: 84549-093 | Form: INJECTION
Manufacturer: ProPharma Distribution
Category: prescription | Type: HUMAN PRESCRIPTION DRUG LABEL
Date: 20251107

ACTIVE INGREDIENTS: PHENYTOIN SODIUM 50 mg/1 mL
INACTIVE INGREDIENTS: PROPYLENE GLYCOL 0.4 mL/1 mL; ALCOHOL 0.1 mL/1 mL; WATER; SODIUM HYDROXIDE

HIGHLIGHTS OF PRESCRIBING INFORMATION

These highlights do not include all the information needed to use PHENYTOIN SODIUM INJECTION safely and effectively. See full prescribing information for PHENYTOIN SODIUM INJECTION.
PHENYTOIN Sodium Injection for intravenous or intramuscular use
Initial U.S. Approval: 1953

WARNING: CARDIOVASCULAR RISK ASSOCIATED WITH RAPID INFUSION

See full prescribing information for complete boxed warning.

- The rate of intravenous Phenytoin Sodium Injection administration should not exceed 50 mg per minute in adults and 1 to 3 mg/kg/min (or 50 mg per minute, whichever is slower) in pediatric patients because of the risk of severe hypotension and cardiac arrhythmias.
- Careful cardiac monitoring is needed during and after administering intravenous Phenytoin Sodium Injection.
- Reduction in rate of administration or discontinuation of dosing may be needed (2.1, 5.1).

RECENT MAJOR CHANGES

Warnings and Precautions (5.3) 02/2021

1 INDICATIONS AND USAGE

Parenteral Phenytoin Sodium Injection is indicated for the treatment of generalized tonic clonic status epilepticus and prevention and treatment of seizures occurring during neurosurgery. Intravenous phenytoin can also be substituted, as short-term use, for oral phenytoin. Parenteral phenytoin should be used only when oral phenytoin administration is not possible. (1)

2 DOSAGE AND ADMINISTRATION

For Status Epilepticus and Non-emergent Loading Dose:

- Adult loading dose is 10 to 15 mg/kg at a rate not exceeding 50 mg/min. (2.2)
- Pediatric loading dose is 15 to 20 mg/kg at a rate not exceeding 1 to 3 mg/kg/min or 50 mg/min, whichever is slower. (2.8)
- Continuous monitoring of the electrocardiogram, blood pressure, and respiratory function is essential. (2.2)

Maintenance Dosing:

- Initial loading dose should be followed by maintenance doses of oral or intravenous Phenytoin Sodium Injection every 6 to 8 hours. (2.2, 2.3)

Intramuscular Administration:

- Because of erratic absorption and local toxicity, Phenytoin Sodium Injection should ordinarily not be given intramuscularly. (2.2, 2.3)

3 DOSAGE FORMS AND STRENGTHS

Injection: 50 mg phenytoin sodium per milliliter in:

- 2 mL and 5 mL single dose vials (3)

4 CONTRAINDICATIONS

Hypersensitivity to phenytoin, its ingredients, or other hydantoins (4)

- Sinus bradycardia, sino-atrial block, second and third degree A-V block, and Adams-Stokes syndrome (4)
- A history of prior acute hepatotoxicity attributable to phenytoin (4, 5.6)
- Coadministration with delavirdine (4)

5 WARNINGS AND PRECAUTIONS

- Withdrawal Precipitated Seizure: May precipitate status epilepticus. Dose reductions or discontinuation should be done gradually. (5.2)
- Serious Dermatologic Reactions: Discontinue phenytoin at the first sign of a rash, unless the rash is clearly not drug-related. If signs or symptoms suggest SJS/TEN, use of this drug should not be resumed and alternative therapy should be considered. (5.3)
- Drug Reaction with Eosinophilia and Systemic Symptoms (DRESS)/Multiorgan hypersensitivity: If signs or symptoms of hypersensitivity are present, evaluate the patient immediately. Discontinue if an alternative etiology cannot be established. (5.4)
- Hematopoietic Complications:If occurs, follow-up observation is indicated and an alternative antiepileptic treatment should be used. (5.7)

6 ADVERSE REACTIONS

The most common adverse reactions are nervous system reactions, including nystagmus, ataxia, slurred speech, decreased coordination, somnolence, and mental confusion. (6)

To report SUSPECTED ADVERSE REACTIONS, contact Hikma Pharmaceuticals USA Inc. at 1-877-845-0689 or FDA at 1-800-FDA-1088 or www.fda.gov/medwatch.

7 DRUG INTERACTIONS

Multiple drug interactions because of extensive plasma protein binding, saturable metabolism and potent induction of hepatic enzymes. (7.1, 7.2)

8 USE IN SPECIFIC POPULATIONS

- Pregnancy: Prenatal exposure to phenytoin may increase the risks for congenital malformations and other adverse developmental outcomes. (5.11, 8.1)
- Renal and/or Hepatic Impairment or Hypoalbuminemia: Monitor unbound phenytoin concentrations in these patients. (8.6)

FULL PRESCRIBING INFORMATION

WARNING: CARDIOVASCULAR RISK ASSOCIATED WITH RAPID INFUSION

The rate of intravenous Phenytoin Sodium Injection administration should not exceed 50 mg per minute in adults and 1 to 3 mg/kg/min (or 50 mg per minute, whichever is slower) in pediatric patients because of the risk of severe hypotension and cardiac arrhythmias. Careful cardiac monitoring is needed during and after administering intravenous Phenytoin Sodium Injection. Although the risk of cardiovascular toxicity increases with infusion rates above the recommended infusion rate, these events have also been reported at or below the recommended infusion rate. Reduction in rate of administration or discontinuation of dosing may be needed [see Dosage and Administration (2.1) and Warnings and Precautions (5.1)].

1 INDICATIONS AND USAGE

Parenteral Phenytoin Sodium Injection is indicated for the treatment of generalized tonic-clonic status epilepticus, and prevention and treatment of seizures occurring during neurosurgery. Intravenous phenytoin can also be substituted, as short-term use, for oral phenytoin. Parenteral phenytoin should be used only when oral phenytoin administration is not possible [see Dosage and Administration (2.1,2.3) and Warnings and Precautions (5.1)] .

2 DOSAGE AND ADMINISTRATION

2.1 General Dosing Information

Because of the increased risk of adverse cardiovascular reactions associated with rapid administration, intravenous administration should not exceed 50 mg per minute in adults. In pediatric patients, the drug should be administered at a rate not exceeding 1 to 3 mg/kg/min or 50 mg per minute, whichever is slower.

As non-emergency therapy, Phenytoin Sodium Injection should be administered more slowly as either a loading dose or by intermittent infusion. Because of the risks of cardiac and local toxicity associated with intravenous phenytoin, oral phenytoin should be used whenever possible.

Because adverse cardiovascular reactions have occurred during and after infusions, careful cardiac monitoring is needed during and after the administration of intravenous Phenytoin Sodium Injection. Reduction in rate of administration or discontinuation of dosing may be needed.

Because of the risk of local toxicity, intravenous Phenytoin Sodium Injection should be administered directly into a large peripheral or central vein through a large-gauge catheter. Prior to the administration, the patency of the intravenous (IV) catheter should be tested with a flush of sterile saline. Each injection of parenteral Phenytoin Sodium Injection should then be followed by a flush of sterile saline through the same catheter to avoid local venous irritation due to the alkalinity of the solution.

Phenytoin Sodium Injection can be given diluted with normal saline. The addition of parenteral Phenytoin Sodium Injection to dextrose and dextrose-containing solutions should be avoided due to lack of solubility and resultant precipitation.

Treatment with Phenytoin Sodium Injection can be initiated either with a loading dose or an infusion:

Loading Dose:A loading dose of parenteral Phenytoin Sodium Injection should be injected slowly, not exceeding 50 mg per minute in adults and 1 to 3 mg/kg/min (or 50 mg per minute, whichever is slower) in pediatric patients.

Infusion:For infusion administration, parenteral Phenytoin Sodium Injection should be diluted in normal saline with the final concentration of phenytoin sodium in the solution no less than 5 mg/mL. Administration should commence immediately after the mixture has been prepared and must be completed within 1 to 4 hours (the infusion mixture should not be refrigerated). An in-line filter (0.22 to 0.55 microns) should be used.

Parenteral drug products should be inspected visually for particulate matter and discoloration prior to administration, whenever solution or container permit.

The diluted infusion mixture (Phenytoin Sodium Injection plus normal saline) should not be refrigerated. If the undiluted parenteral Phenytoin Sodium Injection is refrigerated or frozen, a precipitate might form: this will dissolve again after the solution is allowed to stand at room temperature. The product is still suitable for use. A faint yellow coloration may develop, however this has no effect on the potency of the solution.

For single-dose only. After opening, any unused product should be discarded.

Monitoring Levels:Trough levels provide information about clinically effective serum level range and are obtained just prior to the patient’s next scheduled dose. Peak levels indicate an individual’s threshold for emergence of dose-related side effects and are obtained at the time of expected peak concentration. Therapeutic effect without clinical signs of toxicity occurs more often with serum total concentrations between 10 and 20 mcg/mL (unbound phenytoin concentrations of 1 to 2 mcg/mL), although some mild cases of tonic-clonic (grand mal) epilepsy may be controlled with lower serum levels of phenytoin. In patients with renal or hepatic disease, or in those with hypoalbuminemia, the monitoring of unbound phenytoin concentrations may be more relevant [see Dosage and Administration (2.3)] .

2.2 Status Epilepticus

In adults, a loading dose of 10 to 15 mg/kg should be administered slowly intravenously, at a rate not exceeding 50 mg per minute (this will require approximately 20 minutes in a 70-kg patient). The loading dose should be followed by maintenance doses of 100 mg orally or intravenously every 6 to 8 hours.

In the pediatric population, a loading dose of 15 to 20 mg/kg of phenytoin sodium intravenously will usually produce serum concentrations of phenytoin within the generally accepted serum total concentrations between 10 and 20 mcg/mL (unbound phenytoin concentrations of 1 to 2 mcg/mL). The drug should be injected slowly intravenously at a rate not exceeding 1 to 3 mg/kg/min or 50 mg per minute, whichever is slower.

Continuous monitoring of the electrocardiogram and blood pressure is essential. The patient should be observed for signs of respiratory depression.

Determination of phenytoin serum levels is advised when using phenytoin in the management of status epilepticus and in the subsequent establishment of maintenance dosage.

Other measures, including concomitant administration of an intravenous benzodiazepine such as diazepam, or an intravenous short-acting barbiturate, will usually be necessary for rapid control of seizures because of the required slow rate of administration of phenytoin.

If administration of parenteral Phenytoin Sodium Injection does not terminate seizures, the use of other anticonvulsants, intravenous barbiturates, general anesthesia, and other appropriate measures should be considered.

Intramuscular administration should not be used in the treatment of status epilepticus because the attainment of peak serum levels may require up to 24 hours.

2.3 Non-emergent Loading and Maintenance Dosing

Because of the risks of cardiac and local toxicity associated with intravenous phenytoin, oral phenytoin should be used whenever possible. In adults, a loading dose of 10 to 15 mg/kg should be administered slowly. The rate of intravenous administration should not exceed 50 mg per minute in adults and 1 to 3 mg/kg/min (or 50 mg per minute, whichever is slower) in pediatric patients. Slower administration rates are recommended to minimize the cardiovascular adverse reactions. Continuous monitoring of the electrocardiogram, blood pressure, and respiratory function is essential.

The loading dose should be followed by maintenance doses of oral or intravenous phenytoin every 6 to 8 hours.

Ordinarily, Phenytoin Sodium Injection should not be given intramuscularly because of the risk of necrosis, abscess formation, and erratic absorption. If intramuscular administration is required, compensating dosage adjustments are necessary to maintain therapeutic serum levels. An intramuscular dose 50% greater than the oral dose is necessary to maintain these levels. When returned to oral administration, the dose should be reduced by 50% of the original oral dose for one week to prevent excessive serum levels due to sustained release from intramuscular tissue sites.

Monitoring serum levels would help prevent a fall into the subtherapeutic range. Serum blood level determinations are especially helpful when possible drug interactions are suspected.

2.4 Parenteral Substitution for Oral Phenytoin Therapy

When treatment with oral phenytoin is not possible, IV phenytoin can be substituted for oral phenytoin at the same total daily dose. Phenytoin capsules are approximately 90% bioavailable by the oral route. Phenytoin is 100% bioavailable by the IV route. For this reason, serum phenytoin concentrations may increase modestly when IV phenytoin is substituted for oral phenytoin sodium therapy. The rate of administration for IV phenytoin should be no greater than 50 mg per minute in adults and 1 to 3 mg/kg/min (or 50 mg per minute, whichever is slower) in pediatric patients.

When intramuscular administration may be required, a sufficient dose must be administered intramuscularly to maintain the serum level within the therapeutic range. Where oral dosage is resumed following intramuscular usage, the oral dose should be properly adjusted to compensate for the slow, continuing IM absorption to minimize toxic symptoms [see Clinical Pharmacology (12.3)].

Serum concentrations should be monitored and care should be taken when switching a patient from the sodium salt to the free acid form. Phenytoin Sodium Injection is formulated with the sodium salt of phenytoin. Because there is approximately an 8% increase in drug content with the free acid form over that of the sodium salt, dosage adjustments and serum level monitoring may be necessary when switching from a product formulated with the free acid to a product formulated with the sodium salt and vice versa.

2.5 Dosing in Patients with Renal or Hepatic Impairment or Hypoalbuminemia

Because the fraction of unbound phenytoin is increased in patients with renal or hepatic disease, or in those with hypoalbuminemia, the monitoring of phenytoin serum levels should be based on the unbound fraction in those patients.

2.6 Dosing in Geriatrics

Phenytoin clearance is decreased slightly in elderly patients and lower or less frequent dosing may be required [see Clinical Pharmacology (12.3)].

2.7 Dosing During Pregnancy

Decreased serum concentrations of phenytoin may occur during pregnancy because of altered phenytoin pharmacokinetics. Periodic measurement of serum phenytoin concentrations should be performed during pregnancy, and the Phenytoin Sodium Injection dosage should be adjusted as necessary. Postpartum restoration of the original dosage will probably be indicated [see Use in Specific Populations (8.1)]. Because of potential changes in protein binding during pregnancy, the monitoring of phenytoin serum levels should be based on the unbound fraction.

2.8 Dosing in Pediatrics

A loading dose of 15 to 20 mg/kg of Phenytoin Sodium Injection intravenously will usually produce serum concentrations of phenytoin within the generally accepted serum total concentrations between 10 and 20 mcg/mL (unbound phenytoin concentrations of 1 to 2 mcg/mL). The drug should be injected slowly intravenously at a rate not exceeding 1 to 3 mg/kg/min or 50 mg per minute, whichever is slower.

3 DOSAGE FORMS AND STRENGTHS

Phenytoin Sodium Injection, USP: 50 mg phenytoin sodium per milliliter is available as:

- 2 mL (100 mg) Single Dose vials
- 5 mL (250 mg) Single Dose vials

4 CONTRAINDICATIONS

Phenytoin Sodium Injection is contraindicated in patients with:

- A history of hypersensitivity to phenytoin, its inactive ingredients, or other hydantoins [see Warnings and Precautions (5.5)] .
- Sinus bradycardia, sino-atrial block, second and third degree A-V block, and Adams-Stokes syndrome because of the effect of parenteral phenytoin on ventricular automaticity.
- A history of prior acute hepatotoxicity attributable to phenytoin [see Warnings and Precautions (5.6)].
- Coadministration with delavirdine because of the potential for loss of virologic response and possible resistance to delavirdine or to the class of non-nucleoside reverse transcriptase inhibitors

5 WARNINGS AND PRECAUTIONS

5.1 Cardiovascular Risk Associated with Rapid Infusion

Rapid intravenous administration of Phenytoin Sodium Injection increases the risk of adverse cardiovascular reactions, including severe hypotension and cardiac arrhythmias. Cardiac arrhythmias have included bradycardia, heart block, ventricular tachycardia, and ventricular fibrillation which have resulted in asystole, cardiac arrest, and death. Severe complications are most commonly encountered in critically ill patients, elderly patients, and patients with hypotension and severe myocardial insufficiency. However, cardiac events have also been reported in adults and children without underlying cardiac disease or comorbidities and at recommended doses and infusion rates.

Intravenous administration should not exceed 50 mg per minute in adults. In pediatric patients, administer the drug at a rate not exceeding 1 to 3 mg/kg/min or 50 mg per minute, whichever is slower.

Although the risk of cardiovascular toxicity increases with infusion rates above the recommended infusion rate, these events have also been reported at or below the recommended infusion rate.

As non-emergency therapy, Phenytoin Sodium Injection should be administered more slowly as either a loading dose or by intermittent infusion. Because of the risks of cardiac and local toxicity associated with intravenous phenytoin, oral phenytoin should be used whenever possible.

Because adverse cardiovascular reactions have occurred during and after infusions, careful cardiac and respiratory monitoring is needed during and after the administration of intravenous Phenytoin Sodium Injection. Reduction in rate of administration or discontinuation of dosing may be needed.

5.2 Withdrawal Precipitated Seizure, Status Epilepticus

Antiepileptic drugs should not be abruptly discontinued because of the possibility of increased seizure frequency, including status epilepticus. When, in the judgment of the clinician, the need for dosage reduction, discontinuation, or substitution of alternative antiepileptic medication arises, this should be done gradually. However, in the event of an allergic or hypersensitivity reaction, rapid substitution of alternative therapy may be necessary. In this case, alternative therapy should be an antiepileptic drug not belonging to the hydantoin chemical class.

5.3 Serious Dermatologic Reactions

Serious and sometimes fatal dermatologic reactions, including toxic epidermal necrolysis (TEN) and Stevens-Johnson syndrome (SJS), have been reported with phenytoin treatment. The onset of symptoms is usually within 28 days, but can occur later. Phenytoin should be discontinued at the first sign of a rash, unless the rash is clearly not drug-related. If signs or symptoms suggest SJS/TEN, use of this drug should not be resumed and alternative therapy should be considered. If a rash occurs, the patient should be evaluated for signs and symptoms of Drug Reaction with Eosinophilia and Systemic Symptoms (DRESS) [see Warnings and Precautions (5.4)] .

Studies in patients of Chinese ancestry have found a strong association between the risk of developing SJS/TEN and the presence of HLA-B*1502, an inherited allelic variant of the HLA B gene, in patients using carbamazepine. Limited evidence suggests that HLA-B*1502 may be a risk factor for the development of SJS/TEN in patients of Asian ancestry taking other antiepileptic drugs associated with SJS/TEN, including phenytoin.In addition, retrospective, case-control, genome-wide association studies in patients of southeast Asian ancestry have also identified an increased risk of SCARs in carriers of the decreased function CYP2C9*3 variant, which has also been associated with decreased clearance of phenytoin. Consider avoiding Phenytoin Sodium Injection as an alternative to carbamazepine in patients who are positive for HLA-B*1502 or in CYP2C9*3 carriers [see Use in Specific Populations (8.7) and Clinical Pharmacology (12.5)] .

The use of HLA-B*1502 orCYP2C9genotyping has important limitations and must never substitute for appropriate clinical vigilance and patient management. The role of other possible factors in the development of, and morbidity from, SJS/TEN, such as antiepileptic drug (AED) dose, compliance, concomitant medications, comorbidities, and the level of dermatologic monitoring have not been studied.

5.4 Drug Reaction with Eosinophilia and Systemic Symptoms (DRESS)/Multiorgan Hypersensitivity

Drug Reaction with Eosinophilia and Systemic Symptoms (DRESS), also known as Multiorgan Hypersensitivity, has been reported in patients taking antiepileptic drugs, including phenytoin. Some of these events have been fatal or life-threatening. DRESS typically, although not exclusively, presents with fever, rash, lymphadenopathy, and/or facial swelling, in association with other organ system involvement, such as hepatitis, nephritis, hematological abnormalities, myocarditis, or myositis sometimes resembling an acute viral infection. Eosinophilia is often present. Because this disorder is variable in its expression, other organ systems not noted here may be involved. It is important to note that early manifestations of hypersensitivity, such as fever or lymphadenopathy, may be present even though rash is not evident. If such signs or symptoms are present, the patient should be evaluated immediately. Phenytoin Sodium Injection should be discontinued if an alternative etiology for the signs or symptoms cannot be established.

5.5 Hypersensitivity

Phenytoin and other hydantoins are contraindicated in patients who have experienced phenytoin hypersensitivity [see Contraindications (4)] . Additionally, consider alternatives to structurally similar drugs such as carboxamides (e.g., carbamazepine), barbiturates, succinimides, and oxazolidinediones (e.g., trimethadione) in these same patients. Similarly, if there is a history of hypersensitivity reactions to these structurally similar drugs in the patient or immediate family members, consider alternatives to phenytoin.

5.6 Hepatic Injury

Cases of acute hepatotoxicity, including infrequent cases of acute hepatic failure, have been reported with phenytoin. These events may be part of the spectrum of DRESS or may occur in isolation [see Warnings and Precautions (5.4)]. Other common manifestations include jaundice, hepatomegaly, elevated serum transaminase levels, leukocytosis, and eosinophilia. The clinical course of acute phenytoin hepatotoxicity ranges from prompt recovery to fatal outcomes. In these patients with acute hepatotoxicity, phenytoin should be immediately discontinued and not re-administered.

5.7 Hematopoietic Complications

Hematopoietic complications, some fatal, have occasionally been reported in association with administration of phenytoin. These have included thrombocytopenia, leukopenia, granulocytopenia, agranulocytosis, and pancytopenia with or without bone marrow suppression.

There have been a number of reports suggesting a relationship between phenytoin and the development of lymphadenopathy (local or generalized) including benign lymph node hyperplasia, pseudolymphoma, lymphoma, and Hodgkin's disease. Although a cause and effect relationship has not been established, the occurrence of lymphadenopathy indicates the need to differentiate such a condition from other types of lymph node pathology. Lymph node involvement may occur with or without symptoms and signs resembling DRESS [see Warnings and Precautions (5.4)].

In all cases of lymphadenopathy, follow-up observation for an extended period is indicated and every effort should be made to achieve seizure control using alternative antiepileptic drugs.

5.8 Local Toxicity (Including Purple Glove Syndrome)

Soft tissue irritation and inflammation has occurred at the site of injection with and without extravasation of intravenous phenytoin.

Edema, discoloration and pain distal to the site of injection (described as “purple glove syndrome”) have also been reported following peripheral intravenous phenytoin injection. Soft tissue irritation may vary from slight tenderness to extensive necrosis, and sloughing. The syndrome may not develop for several days after injection. Although resolution of symptoms may be spontaneous, skin necrosis and limb ischemia have occurred and required such interventions as fasciotomies, skin grafting, and, in rare cases, amputation.

Because of the risk of local toxicity, intravenous Phenytoin Sodium Injection should be administered directly into a large peripheral or central vein through a large-gauge catheter. Prior to the administration, the patency of the IV catheter should be tested with a flush of sterile saline. Each injection of parenteral Phenytoin Sodium Injection should then be followed by a flush of sterile saline through the same catheter to avoid local venous irritation caused by the alkalinity of the solution.

Intramuscular Phenytoin Sodium Injection administration may cause pain, necrosis, and abscess formation at the injection site [see Dosage and Administration (2.3)] .

5.9 Renal or Hepatic Impairment or Hypoalbuminemia

Because the fraction of unbound phenytoin is increased in patients with renal or hepatic disease, or in those with hypoalbuminemia, the monitoring of phenytoin serum levels should be based on the unbound fraction in those patients.

5.10 Exacerbation of Porphyria

In view of isolated reports associating phenytoin with exacerbation of porphyria, caution should be exercised in using this medication in patients suffering from this disease.

5.11 Teratogenicity and Other Harm to the Newborn

Phenytoin Sodium Injection may cause fetal harm when administered to a pregnant woman. Prenatal exposure to phenytoin may increase the risks for congenital malformations and other adverse developmental outcomes [see Use in Specific Populations (8.1)] .

Increased frequencies of major malformations (such as orofacial clefts and cardiac defects), and abnormalities characteristic of fetal hydantoin syndrome, including dysmorphic skull and facial features, nail and digit hypoplasia, growth abnormalities (including microcephaly), and cognitive deficits, have been reported among children born to epileptic women who took phenytoin alone or in combination with other antiepileptic drugs during pregnancy. There have been several reported cases of malignancies, including neuroblastoma.

A potentially life-threatening bleeding disorder related to decreased levels of vitamin K-dependent clotting factors may occur in newborns exposed to phenytoin in utero. This drug-induced condition can be prevented with vitamin K administration to the mother before delivery and to the neonate after birth.

5.12 Hyperglycemia

Hyperglycemia, resulting from the drug's inhibitory effect on insulin release, has been reported. Phenytoin may also raise the serum glucose level in diabetic patients.

5.13 Serum Phenytoin Levels Above Therapeutic Range

Serum levels of phenytoin sustained above the therapeutic range may produce confusional states referred to as "delirium", "psychosis", or "encephalopathy", or rarely irreversible cerebellar dysfunction and/or cerebellar atrophy. Accordingly, at the first sign of acute toxicity, serum levels should be immediately checked. Dose reduction of phenytoin therapy is indicated if serum levels are excessive; if symptoms persist, termination is recommended.

6 ADVERSE REACTIONS

The following serious adverse reactions are described elsewhere in the labeling:

- Cardiovascular Risk Associated with Rapid Infusion [see Warnings and Precautions (5.1)]
- Withdrawal Precipitated Seizure, Status Epilepticus [see Warnings and Precautions (5.2)]
- Serious Dermatologic Reactions [see Warnings and Precautions (5.3)]
- Drug Reaction with Eosinophilia and Systemic Symptoms (DRESS)/Multiorgan Hypersensitivity [see Warnings and Precautions (5.4)]
- Hypersensitivity [see Warnings and Precautions (5.5)]
- Hepatic Injury [see Warnings and Precautions (5.6)]
- Hematopoietic Complications [see Warnings and Precautions (5.7)]
- Local toxicity (Including Purple Glove Syndrome) [see Warnings and Precautions (5.8)]
- Exacerbation of Porphyria [see Warnings and Precautions (5.10)]
- Teratogenicity and Other Harm to the Newborn [see Warnings and Precautions (5.11)]
- Hyperglycemia [see Warnings and Precautions (5.12)]

The following adverse reactions associated with the use of Phenytoin Sodium Injection were identified in clinical studies or postmarketing reports. Because these reactions are reported voluntarily from a population of uncertain size, it is not always possible to reliably estimate their frequency or establish a causal relationship to drug exposure.

The most notable signs of toxicity associated with the intravenous use of this drug are cardiovascular collapse and/or CNS depression. Hypotension does occur when the drug is administered rapidly by the intravenous route. The rate of administration is very important; it should not exceed 50 mg per minute in adults, and 1 to 3 mg/kg/min (or 50 mg per minute, whichever is slower) in pediatric patients [see Boxed Warning, Dosage and Administration (2.1),and Warnings and Precautions (5.1)] .

Body As a Whole:Allergic reactions in the form of rash and rarely more serious forms (see Skin and Appendages paragraph below) and DRESS [see Warnings and Precautions (5.4)] have been observed. Anaphylaxis has also been reported.

There have also been reports of coarsening of facial features, systemic lupus erythematosus, periarteritis nodosa, and immunoglobulin abnormalities.

Cardiovascular:Severe cardiovascular events and fatalities have been reported with atrial and ventricular conduction depression and ventricular fibrillation. Severe complications are most commonly encountered in elderly or critically ill patients [see Boxed Warning and Warnings and Precautions (5.1)].

Digestive System:Acute hepatic failure [see Warnings and Precautions (5.6)] , toxic hepatitis, liver damage, nausea, vomiting, constipation, enlargement of the lips, and gingival hyperplasia.

Hematologic and Lymphatic System:Hematopoietic complications, some fatal, have occasionally been reported in association with administration of phenytoin [see Warnings and Precautions (5.7)] . These have included thrombocytopenia, leukopenia, granulocytopenia, agranulocytosis, and pancytopenia with or without bone marrow suppression. While macrocytosis and megaloblastic anemia have occurred, these conditions usually respond to folic acid therapy. Lymphadenopathy, including benign lymph node hyperplasia, pseudolymphoma, lymphoma, and Hodgkin's Disease have been reported [see Warnings and Precautions (5.7)].

Laboratory Test Abnormality:Phenytoin may decrease serum concentrations of thyroid hormone (T4 and T3), sometimes with an accompanying increase in thyroid-stimulating hormone (TSH), but usually in the absence of clinical hypothyroidism. Phenytoin may also produce lower than normal values for dexamethasone or metyrapone tests. Phenytoin may also cause increased serum levels of glucose ,alkaline phosphatase, and gamma glutamyl transpeptidase (GGT).

Nervous System:The most common adverse reactions encountered with phenytoin therapy are nervous system reactions and are usually dose-related. Reactions include nystagmus, ataxia, slurred speech, decreased coordination, somnolence, and mental confusion. Dizziness, vertigo, insomnia, transient nervousness, motor twitchings, paresthesia, and headaches have also been observed. There have also been rare reports of phenytoin induced dyskinesias, including chorea, dystonia, tremor and asterixis, similar to those induced by phenothiazine and other neuroleptic drugs. Cerebellar atrophy has been reported, and appears more likely in settings of elevated phenytoin levels and/or long-term phenytoin use [see Warnings and Precautions (5.13)] .

A predominantly sensory peripheral polyneuropathy has been observed in patients receiving long-term phenytoin therapy.

Skin and Appendages:Dermatological manifestations sometimes accompanied by fever have included scarlatiniform or morbilliform rashes. A morbilliform rash (measles-like) is the most common; other types of dermatitis are seen more rarely. Other more serious forms which may be fatal have included bullous, exfoliative or purpuric dermatitis, Stevens-Johnson syndrome, and toxic epidermal necrolysis [see Warnings and Precautions (5.3)] . There have also been reports of hypertrichosis.

Local irritation, inflammation, tenderness, necrosis, and sloughing have been reported with or without extravasation of intravenous phenytoin [see Warnings and Precautions (5.8)] .

Special Senses:Altered taste sensation including metallic taste.

Urogenital:Peyronie’s disease

7 DRUG INTERACTIONS

Phenytoin is extensively bound to plasma proteins and is prone to competitive displacement. Phenytoin is primarily metabolized by hepatic cytochrome P450 enzymes CYP2C9 and to a lesser extent by CYP2C19 and is particularly susceptible to inhibitory drug interactions because it is subject to saturable metabolism. Inhibition of metabolism may produce significant increases in circulating phenytoin concentrations and enhance the risk of drug toxicity. Monitoring of phenytoin serum levels is recommended when a drug interaction is suspected.

Phenytoin is a potent inducer of hepatic drug-metabolizing enzymes.

7.1 Drugs That Affect Phenytoin Concentrations

Table 1 includes commonly occurring drug interactions that affect phenytoin concentrations. However, this list is not intended to be inclusive or comprehensive. Individual prescribing information from relevant drugs should be consulted.

The addition or withdrawal of these agents in patients on phenytoin therapy may require an adjustment of the phenytoin dose to achieve optimal clinical outcome.

Table 1: Drugs That Affect Phenytoin Concentrations

Interacting Agent | Examples
Drugs that may increase phenytoin serum levels
Antiepileptic drugs | Ethosuximide, felbamate, oxcarbazepine, methsuximide, topiramate
Azoles | Fluconazole, ketoconazole, itraconazole, miconazole, voriconazole
Antineoplastic agents | Capecitabine, fluorouracil
Antidepressants | Fluoxetine, fluvoxamine, sertraline
Gastric acid reducing agents | H2antagonists (cimetidine), omeprazole
Sulfonamides | Sulfamethizole, sulfaphenazole, sulfadiazine, sulfamethoxazole trimethoprim
Other | Acute alcohol intake, amiodarone, chloramphenicol, chlordiazepoxide, disulfiram, estrogen, fluvastatin, isoniazid, methylphenidate, phenothiazines, salicylates, ticlopidine, tolbutamide, trazodone, warfarin
Drugs that may decrease phenytoin serum levels
Antineoplastic agents usually in combination | Bleomycin, carboplatin, cisplatin, doxorubicin, methotrexate
Antiviral agents | Fosamprenavir, nelfinavir, ritonavir
Antiepileptic drugs | Carbamazepine, vigabatrin
Other | Chronic alcohol abuse, diazepam, diazoxide, folic acid, reserpine, rifampin, St. John’s wortb, theophylline
Drugs that may either increase or decrease phenytoin serum levels
Antiepileptic drugs | Phenobarbital, valproate sodium, valproic acid

bThe induction potency of St. John’s wort may vary widely based on preparation.

7.2 Drugs Affected by Phenytoin

Table 2 includes commonly occurring drug interactions affected by phenytoin. However, this list is not intended to be inclusive or comprehensive. Individual drug package inserts should be consulted. The addition or withdrawal of phenytoin during concomitant therapy with these agents may require adjustment of the dose of these agents to achieve optimal clinical outcome.

Table 2: Drugs Affected by Phenytoin

Interacting Agent | Examples
Drugs whose efficacy is impaired by phenytoin
Azoles | Fluconazole, ketoconazole, itraconazole, posaconazole, voriconazole
Antineoplastic agents | Irinotecan, paclitaxel, teniposide
Delavirdine | Phenytoin can substantially reduce the concentrations of delavirdine. This can lead to loss of virologic response and possible resistance [see Contraindications (4)].
Neuromuscular blocking agents | Cisatracurium, pancuronium, rocuronium and vecuronium: resistance to the neuromuscular blocking action of the nondepolarizing neuromuscular blocking agents has occurred in patients chronically administered phenytoin. Whether or not phenytoin has the same effect on other non-depolarizing agents is unknown.; Prevention or Management: Patients should be monitored closely for more rapid recovery from neuromuscular blockade than expected, and infusion rate requirements may be higher.
Warfarin | Increased and decreased PT/INR responses have been reported when phenytoin is coadministered with warfarin
Other | Corticosteroids, doxycycline, estrogens, furosemide, oral contraceptives, paroxetine, quinidine, rifampin, sertraline, theophylline, and vitamin D
Drugs whose level is decreased by phenytoin
Antiepileptic drugsa | Carbamazepine, felbamate, lamotrigine, topiramate, oxcarbazepine
Antilipidemic agents | Atorvastatin, fluvastatin, simvastatin
Antiviral agents | Efavirenz, lopinavir/ritonavir, indinavir, nelfinavir, ritonavir, saquinavir; Fosamprenavir: phenytoin when given with fosamprenavir alone may decrease the concentration of amprenavir, the active metabolite. Phenytoin when given with the combination of fosamprenavir and ritonavir may increase the concentration of amprenavir
Calcium channel blockers | Nifedipine, nimodipine, nisoldipine, verapamil
Other | Albendazole (decreases active metabolite), chlorpropamide, clozapine, cyclosporine, digoxin, disopyramide, folic acid, methadone, mexiletine, praziquantel, quetiapine

aThe effect of phenytoin on phenobarbital, valproic acid and sodium valproate serum levels is unpredictable

7.3 Drug/Laboratory Test Interactions

Care should be taken when using immunoanalytical methods to measure serum phenytoin concentrations following fosphenytoin administration.

8 USE IN SPECIFIC POPULATIONS

8.1 Pregnancy

Pregnancy Exposure Registry

There is a pregnancy exposure registry that monitors pregnancy outcomes in women exposed to antiepileptic drugs (AEDs), such as Phenytoin Sodium Injection, during pregnancy. Physicians are advised to recommend that pregnant patients taking phenytoin enroll in the North American Antiepileptic Drug (NAAED) Pregnancy Registry. This can be done by calling the toll free number 1-888-233-2334, and must be done by patients themselves. Information on the registry can also be found at the website http://www.aedpregnancyregistry.org/.

Risk Summary

In humans, prenatal exposure to phenytoin may increase the risks for congenital malformations and other adverse developmental outcomes. Prenatal phenytoin exposure is associated with an increased incidence of major malformations (including orofacial clefts and cardiac defects). In addition, the fetal hydantoin syndrome a pattern of abnormalities including dysmorphic skull and facial features, nail and digit hypoplasia, growth abnormalities (including microcephaly), and cognitive deficits has been reported among children born to epileptic women who took phenytoin alone or in combination with other antiepileptic drugs during pregnancy [see Data] . There have been several reported cases of malignancies, including neuroblastoma, in children whose mothers received phenytoin during pregnancy.

Administration of phenytoin to pregnant animals resulted in an increased incidence of fetal malformations and other manifestations of developmental toxicity (including embryofetal death, growth impairment, and behavioral abnormalities) in multiple species at clinically relevant doses [see Data].

In the U.S. general population, the estimated background risk of major birth defects and of miscarriage in clinically recognized pregnancies is 2 to 4% and 15 to 20%, respectively. The background risk of major birth defects and miscarriage for the indicated population is unknown.

Clinical Considerations

Disease-associated maternal risk

An increase in seizure frequency may occur during pregnancy because of altered phenytoin pharmacokinetics. Periodic measurement of serum phenytoin concentrations may be valuable in the management of pregnant women as a guide to appropriate adjustment of dosage [see Dosage and Administration (2.1, 2.7)] . However, postpartum restoration of the original dosage will probably be indicated.

Fetal/Neonatal adverse reactions

A potentially life-threatening bleeding disorder related to decreased levels of vitamin K-dependent clotting factors may occur in newborns exposed to phenytoin in utero. This drug-induced condition can be prevented with vitamin K administration to the mother before delivery and to the neonate after birth.

Data

Human Data

Meta-analyses using data from published observational studies and registries have estimated an approximately 2.4-fold increased risk for any major malformation in children with prenatal phenytoin exposure compared to controls. An increased risk of heart defects, facial clefts, and digital hypoplasia has been reported. The fetal hydantion syndrome is a pattern of congenital anomalies including craniofacial anomalies, nail and digital hypoplasia, prenatal-onset growth deficiency, and neurodevelopmental deficiencies.

Animal Data

Administration of phenytoin to pregnant rats, rabbits, and mice during organogenesis resulted in embryofetal death, fetal malformations, and decreased fetal growth retardation. Malformations (including craniofacial, cardiovascular, neural, limb, and digit abnormalities) were observed in rats, rabbits, and mice at doses as low as 100, 75, and 12.5 mg/kg, respectively.

8.2 Lactation

Risk Summary

Phenytoin is secreted in human milk. The developmental and health benefits of breastfeeding should be considered along with the mother’s clinical need for Phenytoin Sodium Injection and any potential adverse effects on the breastfed infant from Phenytoin Sodium Injection or from the underlying maternal condition.

8.4 Pediatric Use

A loading dose of 15 to 20 mg/kg of Phenytoin Sodium Injection intravenously will usually produce serum concentrations of phenytoin within the generally accepted serum total concentrations between 10 and 20 mcg/mL (unbound phenytoin concentrations of 1 to 2 mcg/mL). Because of the increased risk of adverse cardiovascular reactions associated with rapid administration Phenytoin Sodium Injection should be injected slowly intravenously at a rate not exceeding 1 to 3 mg/kg/min or 50 mg per minute, whichever is slower [see Dosage and Administration (2.8) and Warnings and Precautions (5.1)].

8.5 Geriatric Use

Phenytoin clearance tends to decrease with increasing age [see Clinical Pharmacology (12.3)] . Lower or less frequent dosing may be required [see Dosage and Administration (2.6)].

8.6 Renal and/or Hepatic Impairment or Hypoalbuminemia

The liver is the site of biotransformation. Patients with impaired liver function, elderly patients, or those who are gravely ill may show early toxicity.

Because the fraction of unbound phenytoin is increased in patients with renal or hepatic disease, or in those with hypoalbuminemia, the monitoring of phenytoin serum levels should be based on the unbound fraction in those patients.

8.7 Use in Patients with Decreased CYP2C9 Function

Patients who are intermediate or poor metabolizers of CYP2C9 substrates (e.g.,*1/*3, *2/*2, *3/*3) may exhibit increased phenytoin serum concentrations compared to patients who are normal metabolizers (e.g., *1/*1). Thus, patients who are known to be intermediate or poor metabolizers may ultimately require lower doses of phenytoin to maintain similar steady-state concentrations compared to normal metabolizers. If early signs of dose-related central nervous system (CNS) toxicity develop, serum concentrations should be checked immediately [see Clinical Pharmacology (12.5)] .

10 OVERDOSAGE

The lethal dose in pediatric patients is not known. The lethal dose in adults is estimated to be 2 to 5 grams. The initial symptoms are nystagmus, ataxia, and dysarthria. Other signs are tremor, hyperreflexia, lethargy, slurred speech, blurred vision, nausea, and vomiting. The patient may become comatose and hypotensive. Death is caused by respiratory and circulatory depression.

There are marked variations among individuals with respect to phenytoin serum levels where toxicity may occur. Nystagmus, on lateral gaze, usually appears at 20 mcg/mL, ataxia at 30 mcg/mL, dysarthria and lethargy appear when the serum concentration is over 40 mcg/mL, but as high a concentration as 50 mcg/mL has been reported without evidence of toxicity. As much as 25 times the therapeutic dose has been taken to result in a serum concentration over 100 mcg/mL with complete recovery. Irreversible cerebellar dysfunction and atrophy have been reported.

Treatment:Treatment is nonspecific since there is no known antidote.

The adequacy of the respiratory and circulatory systems should be carefully observed and appropriate supportive measures employed. Hemodialysis can be considered since phenytoin is not completely bound to plasma proteins. Total exchange transfusion has been used in the treatment of severe intoxication in pediatric patients.

In acute overdosage the possibility of other CNS depressants, including alcohol, should be borne in mind.

11 DESCRIPTION

Phenytoin Sodium Injection, USP is a sterile solution containing in each mL phenytoin sodium 50 mg, propylene glycol 0.4 mL and alcohol 0.1 mL in Water for Injection. pH 10.0-12.3; sodium hydroxide added, if needed, for pH adjustment.

Phenytoin sodium is related to the barbiturates in chemical structure, but has a five-membered ring. The chemical name is sodium 5,5-diphenyl-2,4-imidazolidinedione represented by the following structural formula:

C15H11N2NaO2 MW 274.25

12 CLINICAL PHARMACOLOGY

12.1 Mechanism of Action

The precise mechanism by which phenytoin exerts its therapeutic effect has not been established but is thought to involve the voltage-dependent blockade of membrane sodium channels resulting in a reduction in sustained high-frequency neuronal discharges.

12.3 Pharmacokinetics

Absorption

A fall in serum levels may occur when patients are changed from oral to intramuscular administration. The drop is caused by slower absorption, as compared to oral administration, because of the poor water solubility of phenytoin. Intravenous administration is the preferred route for producing rapid therapeutic serum levels.

Patients stabilized on a daily oral regimen of phenytoin experience a drop in peak blood levels to 50 to 60 percent of stable levels if crossed over to an equal dose administered intramuscularly. However, the intramuscular depot of poorly soluble material is eventually absorbed, as determined by urinary excretion of 5-(p-hydroxyphenyl)-5-phenylhydantoin (HPPH), the principal metabolite, as well as the total amount of drug eventually appearing in the blood. As phenytoin is highly protein bound, free phenytoin levels may be altered in patients whose protein binding characteristics differ from normal.

A short-term (one week) study indicates that patients do not experience the expected drop in blood levels when crossed over to the intramuscular route if the phenytoin IM dose is increased by 50 percent over the previously established oral dose. To avoid drug accumulation caused by absorption from the muscle depots, it is recommended that for the first week back on oral phenytoin, the dose be reduced to half of the original oral dose (one-third of the IM dose). Experience for periods greater than one week is lacking and blood level monitoring is recommended.

Therapeutic effect without clinical signs of toxicity occurs most often with serum total concentrations between 10 and 20 mcg/mL (unbound phenytoin concentrations of 1 to 2 mcg/mL).

Distribution

Phenytoin is extensively bound to plasma proteins and is prone to competitive displacement.

Elimination

The serum half-life in man after intravenous administration ranges from 10 to 15 hours.

Metabolism

Phenytoin is metabolized by the hepatic cytochrome P450 enzymes CYP2C9 and to a lesser extent by CYP2C19.

Excretion

Most of the drug is excreted in the bile as inactive metabolites. Urinary excretion of phenytoin and its metabolites occurs partly by glomerular filtration but, more importantly, by tubular secretion.

Specific Populations

Age: Geriatric Population:

Phenytoin clearance tends to decrease with increasing age (20% less in patients over 70 years of age relative to that in patients 20 to 30 years of age). Since phenytoin clearance is decreased slightly in elderly patients, lower or less frequent dosing may be required [see Dosage and Administration (2.6)].

Sex/Race:

Gender and race have no significant impact on phenytoin pharmacokinetics.

Renal or Hepatic Impairment:

Increased fraction of unbound phenytoin in patients with renal or hepatic disease, or in those with hypoalbuminemia has been reported.

Pregnancy:

It has been reported in the literature that the plasma clearance of phenytoin generally increased during pregnancy, reached a peak in the third trimester and returned to the level of pre-pregnancy after few weeks or months of delivery.

Drug Interaction Studies

Phenytoin is primarily metabolized by the cytochrome P450 enzymes CYP2C9 and to a lesser extent by CYP2C19.

Phenytoin is a potent inducer of hepatic drug-metabolizing enzymes [see Drug Interactions (7.1,7.2)] .

12.5 Pharmacogenomics

CYP2C9 activity is decreased in individuals with genetic variants such as the CYP2C9*2 and CYP2C9*3 alleles. Carriers of variant alleles, resulting in intermediate (e.g., *1/*3, *2/*2) or poor metabolism (e.g., *2/*3, *3/*3) have decreased clearance of phenytoin. Other decreased or nonfunctional CYP2C9 alleles may also result in decreased clearance of phenytoin (e.g., *5, *6, *8, *11).
The prevalence of the CYP2C9 poor metabolizer phenotype is approximately 2-3% in the White population, 0.5-4% in the Asian population, and <1 % in the African American population. The CYP2C9 intermediate phenotype prevalence is approximately 35% in the White population, 24% in the African American population, and 15-36% in the Asian population [see Warnings and Precautions (5.3) and Use in Specific Populations (8.7)] .

13 NONCLINICAL TOXICOLOGY

13.1 Carcinogenesis, Mutagenesis, Impairment of Fertility

Carcinogenesis [see Warnings and Precautions (5.7)]

In carcinogenicity studies, phenytoin was administered in the diet to mice (10, 25, or 45 mg/kg/day) and rats (25, 50, or 100 mg/kg/day) for 2 years. The incidences of hepatocellular tumors were increased in male and female mice at the highest dose. No increases in tumor incidence were observed in rats. The highest doses tested in these studies were associated with peak serum phenytoin levels below human therapeutic concentrations.

In carcinogenicity studies reported in the literature, phenytoin was administered in the diet for 2 years at doses up to 600 ppm (approximately 90 mg/kg/day) to mice and up to 2400 ppm (approximately 120 mg/kg/day) to rats. The incidences of hepatocellular tumors were increased in female mice at all but the lowest dose tested. No increases in tumor incidence were observed in rats.

Mutagenesis

Phenytoin was negative in the Ames test and in the in vitroclastogenicity assay in Chinese hamster ovary (CHO) cells.

In studies reported in the literature, phenytoin was negative in the in vitromouse lymphoma assay and the in vivomicronucleus assay in mouse. Phenytoin was clastogenic in the in vitrosister chromatid exchange assay in CHO cells.

Fertility

Phenytoin has not been adequately assessed for effects on male or female fertility.

16 HOW SUPPLIED/STORAGE AND HANDLING

16.1 How Supplied

Phenytoin Sodium Injection, USP—50 mg/mL

2 mL (100 mg) Single Dose vial (NDC 84549-093-25)

16.2 Storage and Handling

For single-dose only. After opening, any unused product should be discarded.

Store at 20° to 25°C (68° to 77°F), excursions permitted to 15° to 30°C (59° to 86°F) [See USP Controlled Room Temperature].

17 PATIENT COUNSELING INFORMATION

Withdrawal of Antiepileptic Drugs

Advise patients not to discontinue use of phenytoin without consulting with their healthcare provider. Phenytoin should normally be gradually withdrawn to reduce the potential for increased seizure frequency and status epilepticus [see Warnings and Precautions (5.2)] .

Potential Signs of Drug Reaction with Eosinophilia and Systemic Symptoms (DRESS) and Other Systemic Reactions

Advise patients of the early toxic signs and symptoms of potential hematologic, dermatologic, hypersensitivity, or hepatic reactions. These symptoms may include, but are not limited to, fever, sore throat, rash, ulcers in the mouth, easy bruising, lymphadenopathy, facial swelling, and petechial or purpuric hemorrhage, and in the case of liver reactions, anorexia, nausea/vomiting, or jaundice. Advise the patient that, because these signs and symptoms may signal a serious reaction, that they must report any occurrence immediately to a physician. In addition, advise the patient that these signs and symptoms should be reported even if mild or when occurring after extended use [see Warnings and Precautions (5.3,5.4, 5.5,5.6, 5.7)] .

Effects of Alcohol Use and Other Drugs and Over-the-Counter Drug Interactions

Caution patients against the use of other drugs or alcoholic beverages without first seeking their physician’s advice [see Warnings and Precautions (5.9) and Drug Interactions (7.1,7.2)] .

Inform patients that certain over-the-counter medications (e.g., cimetidine and omeprazole), vitamins (e.g., folic acid), and herbal supplements (e.g., St. John’s wort) can alter their phenytoin levels.

Hyperglycemia

Advise patients that phenytoin may cause an increase in blood glucose levels [see Warnings and Precautions (5.12)] .

Gingival Hyperplasia

Advise patients of the importance of good dental hygiene in order to minimize the development of gingival hyperplasia and its complications.

Neurologic Effects

Counsel patients that phenytoin may cause dizziness, gait disturbance, decreased coordination and somnolence. Advise patients taking phenytoin not to drive, operate complex machinery, or engage in other hazardous activities until they have become accustomed to any such effects associated with phenytoin.

Use in Pregnancy

Inform pregnant women and women of childbearing potential that use of phenytoin during pregnancy can cause fetal harm, including an increased risk for cleft lip and/or cleft palate (oral clefts), cardiac defects, dysmorphic skull and facial features, nail and digit hypoplasia, growth abnormalities (including microcephaly), and cognitive deficits. When appropriate, counsel pregnant women and women of childbearing potential about alternative therapeutic options. Advise women of childbearing potential who are not planning a pregnancy to use effective contraception while using phenytoin, keeping in mind that there is a potential for decreased hormonal contraceptive efficacy [see Drug Interactions (7.2)].

Instruct patients to notify their physician if they become pregnant or intend to become pregnant during therapy, and to notify their physician if they are breastfeeding or intend to breastfeed during therapy [see Use in Specific Populations (8.1,8.2)] .

Encourage patients to enroll in the North American Antiepileptic Drug (NAAED) Pregnancy Registry if they become pregnant. This registry is collecting information about the safety of antiepileptic drugs during pregnancy [see Use in Specific Populations (8.1)] .

Manufactured by:

Hikma Pharmaceuticals USA Inc.
Berkeley Heights, NJ 07922